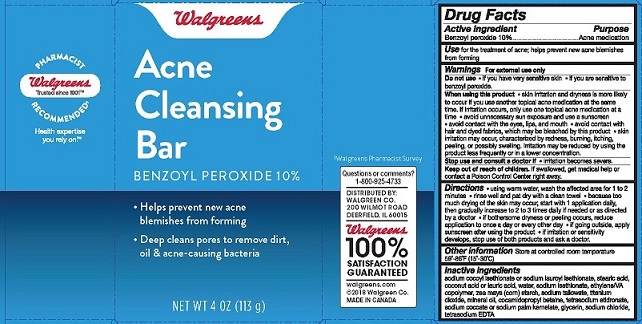 DRUG LABEL: Acne Cleansing Bar
NDC: 0363-0137 | Form: SOAP
Manufacturer: Walgreens
Category: otc | Type: HUMAN OTC DRUG LABEL
Date: 20230124

ACTIVE INGREDIENTS: BENZOYL PEROXIDE 100 mg/1 g
INACTIVE INGREDIENTS: SODIUM COCOYL ISETHIONATE; SODIUM LAUROYL ISETHIONATE; STEARIC ACID; SODIUM TALLOWATE, BEEF; COCONUT ACID; LAURIC ACID; WATER; SODIUM ISETHIONATE; ETHYLENE-VINYL ACETATE COPOLYMER (15% VINYL ACETATE); STARCH, CORN; SODIUM COCOATE; SODIUM PALM KERNELATE; GLYCERIN; TITANIUM DIOXIDE; MINERAL OIL; COCAMIDOPROPYL BETAINE; ETIDRONATE TETRASODIUM; SODIUM CHLORIDE; EDETATE SODIUM

Walgreens Acne Cleansing Bar

Drug Facts

Active ingredient

Benzoyl peroxide 10%

Purpose

Acne medication

INDICATIONS AND USAGE

Use for the treatment of acne; helps prevent new acne blemishes from forming

Warnings

For external use only

Do not use

• if you have very sensitive skin • if you are sensitive to benzoyl peroxide.

When using this product

• skin irritation and dryness is more likely to occur if you use another topical acne medication at the same time. If irritation occurs, only use one topical acne medication at a time • avoid unnecessary sun exposure and use a sunscreen • avoid contact with the eyes, lips, and mouth • avoid contact with hair and dyed fabrics, which may be bleached by this product • skin irritation may occur, characterized by redness, burning, itching, peeling, or possibly swelling. Irritation may be reduced by using the product less frequently or in a lower concentration.

Stop use and ask a doctor if • irritation becomes severe.

Keep out of reach of children. If swallowed, get medical help or contact a Poison Control Center right away.

DOSAGE AND ADMINISTRATION

Directions • using warm water, wash the affected area for 1 to 2 minutes • rinse well and pat dry with a clean towel • because too much drying of the skin may occur, start with 1 application daily, then gradually increase to 2 or 3 times daily if needed or as directed by a doctor • if bothersome dryness or peeling occurs, reduce application to once a day or every other day • if going outside, apply sunscreen after using the product • If irritation or sensitivity develops, stop use of both products and ask a doctor.

Other information Store at controlled room temperature 59° - 86°F (15° - 30°C)

INACTIVE INGREDIENT

Inactive ingredients sodium cocoyl isethionate or sodium lauroyl isethionate, stearic acid, coconut acid or lauric acid, water, sodium isethionate, ethylene/VA copolymer, zea mays (corn) starch, sodium tallowate, titanium dioxide, mineral oil, cocamidopropyl betaine, tetrasodium etidronate, sodium cocoate or sodium palm kernelate, glycerin, sodium chloride, tetrasodium EDTA

Questions or comments?

1-800-925-4733

DISTRIBUTED BY:

WALGREEN CO.

200 WILMOT ROAD

DEERFIELD, IL 60015

Walgreens 100% SATISFACTION GUARANTEED

walgreens.com

©2018 Walgreen Co.

MADE IN CANADA

PACKAGE LABEL

Walgreens

Acne Cleansing Bar

Benzoyl Peroxide 10%

• Helps prevent new acne blemishes from forming
• Deep cleans pores to remove dirt, oil and acne-causing bacteria.

NET WT 4 OZ (113 g)